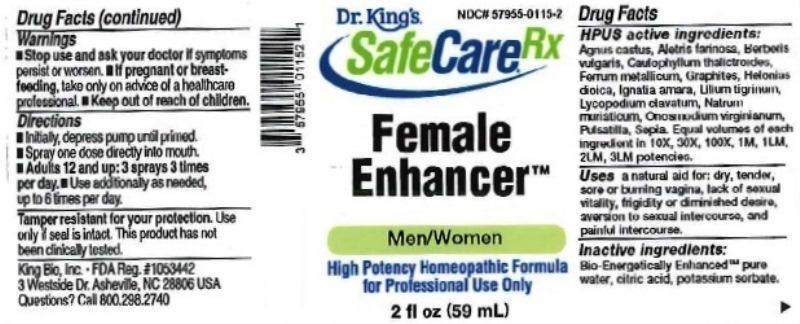 DRUG LABEL: Female Enhancer
NDC: 57955-0115 | Form: LIQUID
Manufacturer: King Bio Inc.
Category: homeopathic | Type: HUMAN OTC DRUG LABEL
Date: 20161103

ACTIVE INGREDIENTS: CHASTE TREE 10 [hp_X]/59 mL; ALETRIS FARINOSA ROOT 10 [hp_X]/59 mL; BERBERIS VULGARIS ROOT BARK 10 [hp_X]/59 mL; CAULOPHYLLUM THALICTROIDES ROOT 10 [hp_X]/59 mL; IRON 10 [hp_X]/59 mL; GRAPHITE 10 [hp_X]/59 mL; CHAMAELIRIUM LUTEUM ROOT 10 [hp_X]/59 mL; STRYCHNOS IGNATII SEED 10 [hp_X]/59 mL; LILIUM LANCIFOLIUM WHOLE FLOWERING 10 [hp_X]/59 mL; LYCOPODIUM CLAVATUM SPORE 10 [hp_X]/59 mL; SODIUM CHLORIDE 10 [hp_X]/59 mL; ONOSMODIUM VIRGINIANUM WHOLE 10 [hp_X]/59 mL; PULSATILLA VULGARIS 10 [hp_X]/59 mL; SEPIA OFFICINALIS JUICE 10 [hp_X]/59 mL
INACTIVE INGREDIENTS: WATER; ANHYDROUS CITRIC ACID; POTASSIUM SORBATE

Female Enhancer™

ACTIVE INGREDIENT

Drug Facts__________________________________________________________________________________________________________

HPUS active ingredients: Agnus castus, Aletris farinosa, Berberis vulgaris, Caulophyllum thalictroides, Ferrum metallicum, Graphites, Helonias dioica, Ignatia amara, Lilium tigrinum, Lycopodium clavatum, Natrum muriaticum, Onosmodium virginianum, Pulsatilla, Sepia. Equal volumes of each ingredient in 10X, 30X, 100X, 1M, 1LM, 2LM, 3LM potencies.

INDICATIONS AND USAGE

Uses: a natural aid for: dry, tender, sore or burning vagina, lack of sexual vitality, frigidity or diminished desire, aversion to sexual intercourse, and painful intercourse.

Inactive Ingredients:

Bio-Energetically Enhanced™ pure water, citric acid and potassium sorbate.

Warnings

- Stop use and ask your doctor if symptoms persist or worsen.
- If pregnant or breast-feeding, take only on advice of a healthcare professional.

- Keep out of reach of children.

Directions

- Initially, depress pump until primed.
- Spray one dose directly into mouth.
- Adults 12 and up: 3 sprays 3 times per day.
- Use additionally as needed, up to 6 times per day.

OTHER SAFETY INFORMATION

Tamper resistant for your protection. Use only if safety seal is intact. This product has not been clinically tested.

PURPOSE

Uses: a natural aid for:

- dry, tender, sore or burning vagina
- lack of sexual vitality
- frigidity or diminished desire
- aversion to sexual intercourse
- painful intercourse